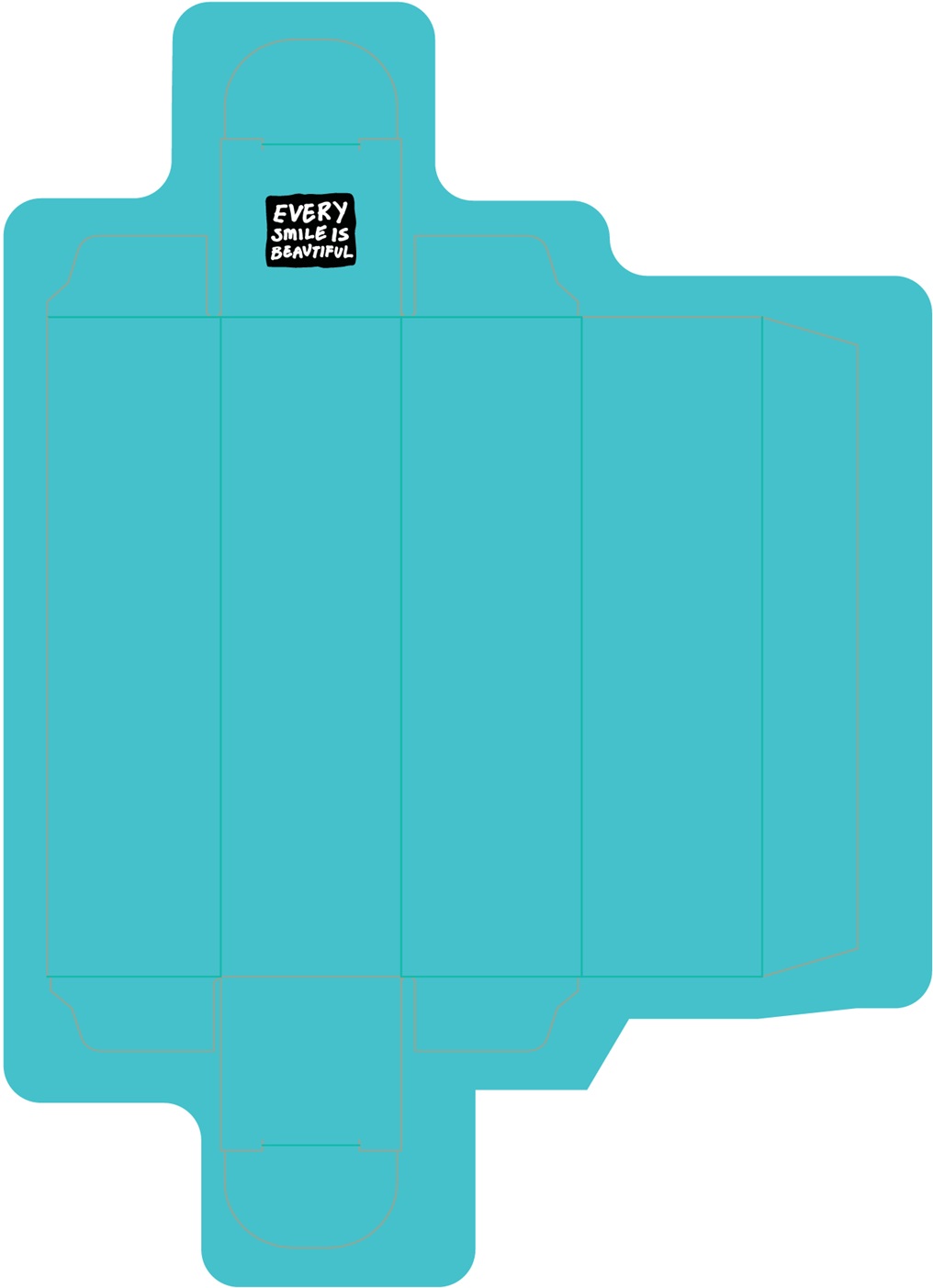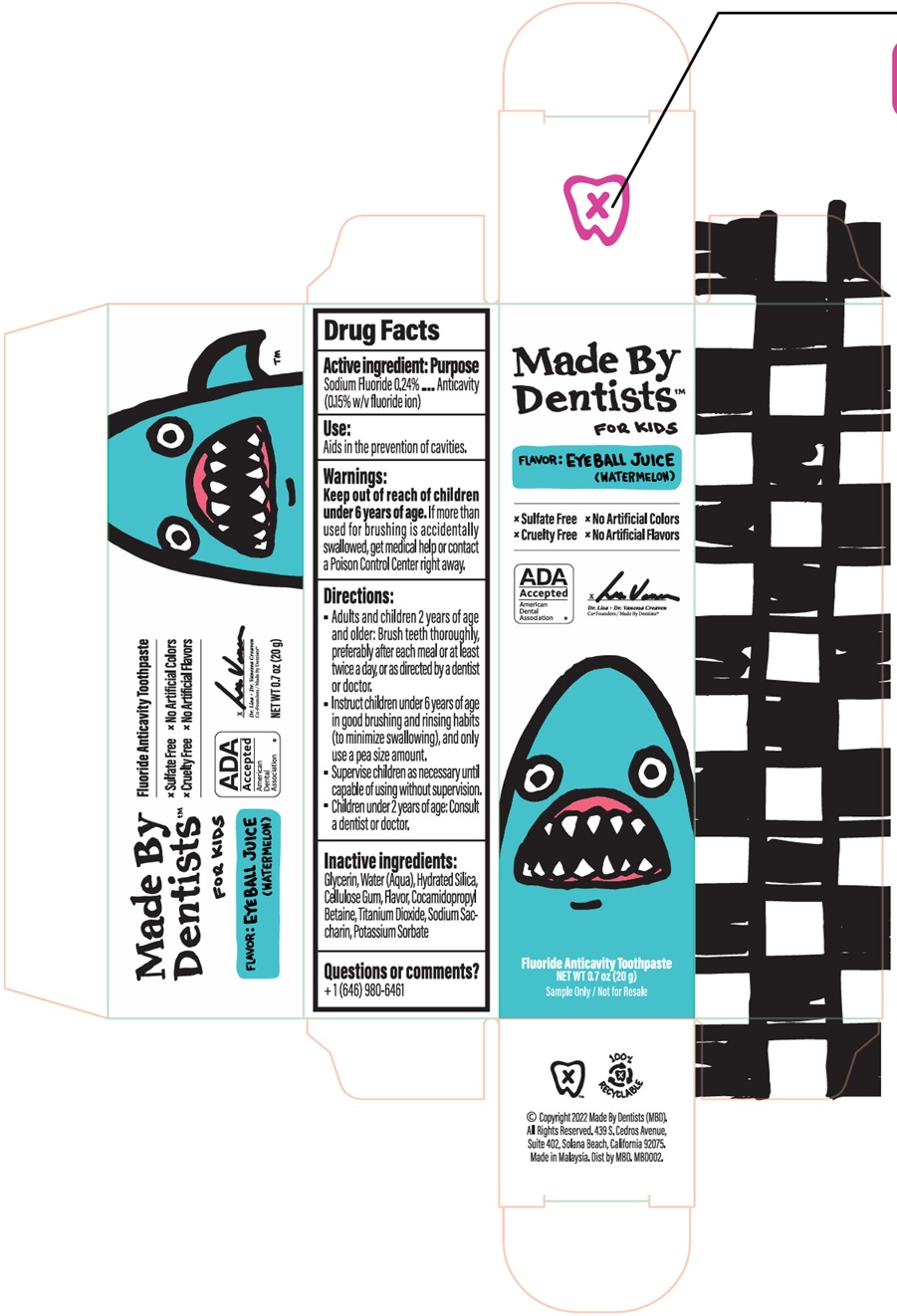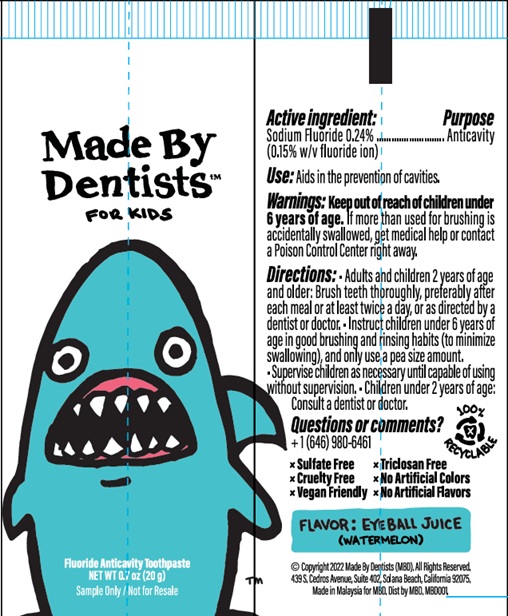 DRUG LABEL: Made by Dentists For Kids Eyeball Juice (Watermelon)
NDC: 75065-030 | Form: PASTE
Manufacturer: MADE BY DENTISTS INC
Category: otc | Type: HUMAN OTC DRUG LABEL
Date: 20260209

ACTIVE INGREDIENTS: SODIUM FLUORIDE 1.5 mg/1 g
INACTIVE INGREDIENTS: WATER; HYDRATED SILICA; GLYCERIN; CARBOXYMETHYLCELLULOSE SODIUM, UNSPECIFIED; COCAMIDOPROPYL BETAINE; POTASSIUM SORBATE; TITANIUM DIOXIDE; SODIUM SACCHARIN

Made by Dentists For Kids Eyeball Juice (Watermelon) Sample Size

Active ingredient:

Sodium Fluoride 0.24% (0.15% w/v fluoride ion)

Purpose

Anticavity

Use:

Aids in the prevention of cavities.

Warnings:

Keep out of reach of children under 6 years of age.

If more than used for brushing is accidentlly swallowed, get medical help or contact a Poison Control Center right away.

Directions:

- Adults and children 2 years of age and older: Brush teeth thoroughly, preferably after each meal or at least twice a day, or as directed by a dentist or doctor.
- Instruct children under 6 years of age in good brushing and rinsing habits (to minimize swallowing), and only use a pea size amount.
- Supervise children as necessary until capable of using without supervision.
- Children under 2 years of age: Consult a dentist or doctor.

Inactive ingredients:

Glycerin, Water (Aqua), Hydrated Silica, Cellulose Gum, Flavor, Cocamidopropyl Betaine, Titanium Dioxide, Sodium Saccharin, Potassium Sorbate

Questions or comments?

+ 1 (646) 980-6461